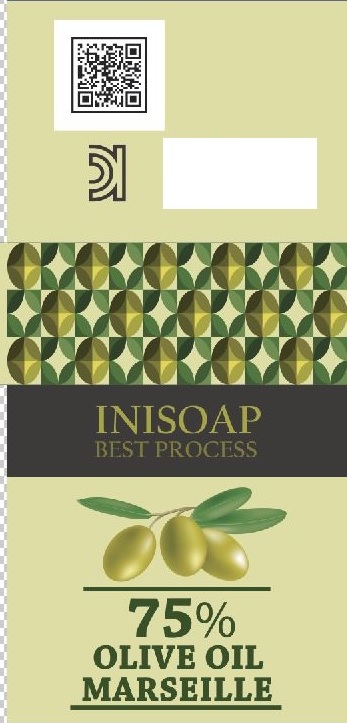 DRUG LABEL: 75% Olive Oil Marseille
NDC: 69836-4001 | Form: SOAP
Manufacturer: International Nature Soap Institute
Category: otc | Type: HUMAN OTC DRUG LABEL
Date: 20160420

ACTIVE INGREDIENTS: GLYCERIN 15 g/100 g
INACTIVE INGREDIENTS: WATER; SODIUM HYDROXIDE; OLIVE OIL

Drug Facts

ACTIVE INGREDIENT

glycerine

INACTIVE INGREDIENT

coconut oil, palm oil, olive oil, sodium hydroxide, water, etc

PURPOSE

skin protectant

keep out of reach of the children

INDICATIONS AND USAGE

apply to the skin and wash away

WARNINGS

・Stop using the product when you have skin problems or the product disagrees with your skin
・Stop using the product immediately and consult a dermatologist if you have redness, swelling, itching or irritation on the skin while or after using the product.
・If the product gets into the eyes, don't rub but rinse with water.
・Don't place the product in any place where it will be subjected to extremely high or low temperatures or direct sunlight.

DOSAGE AND ADMINISTRATION

for external use only